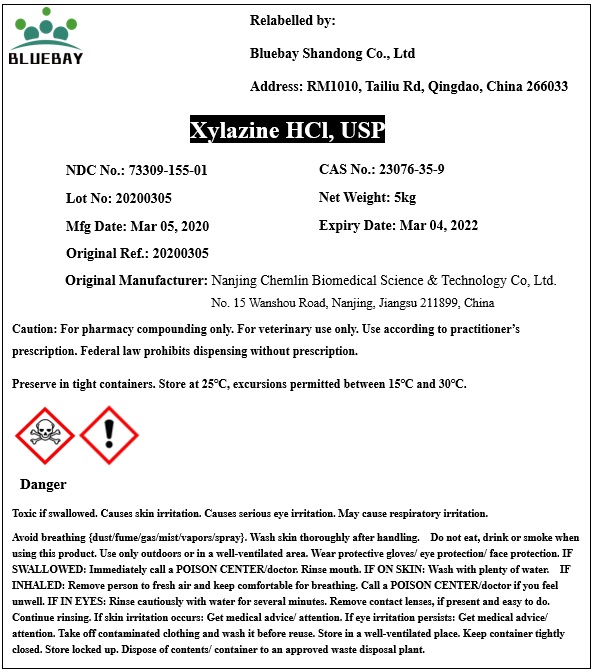 DRUG LABEL: Xylazine HCl
NDC: 73309-155 | Form: POWDER
Manufacturer: BLUEBAY SHANDONG CO.,LTD
Category: other | Type: BULK INGREDIENT
Date: 20200703

ACTIVE INGREDIENTS: XYLAZINE HYDROCHLORIDE 1 kg/1 kg

Xylazine HCl